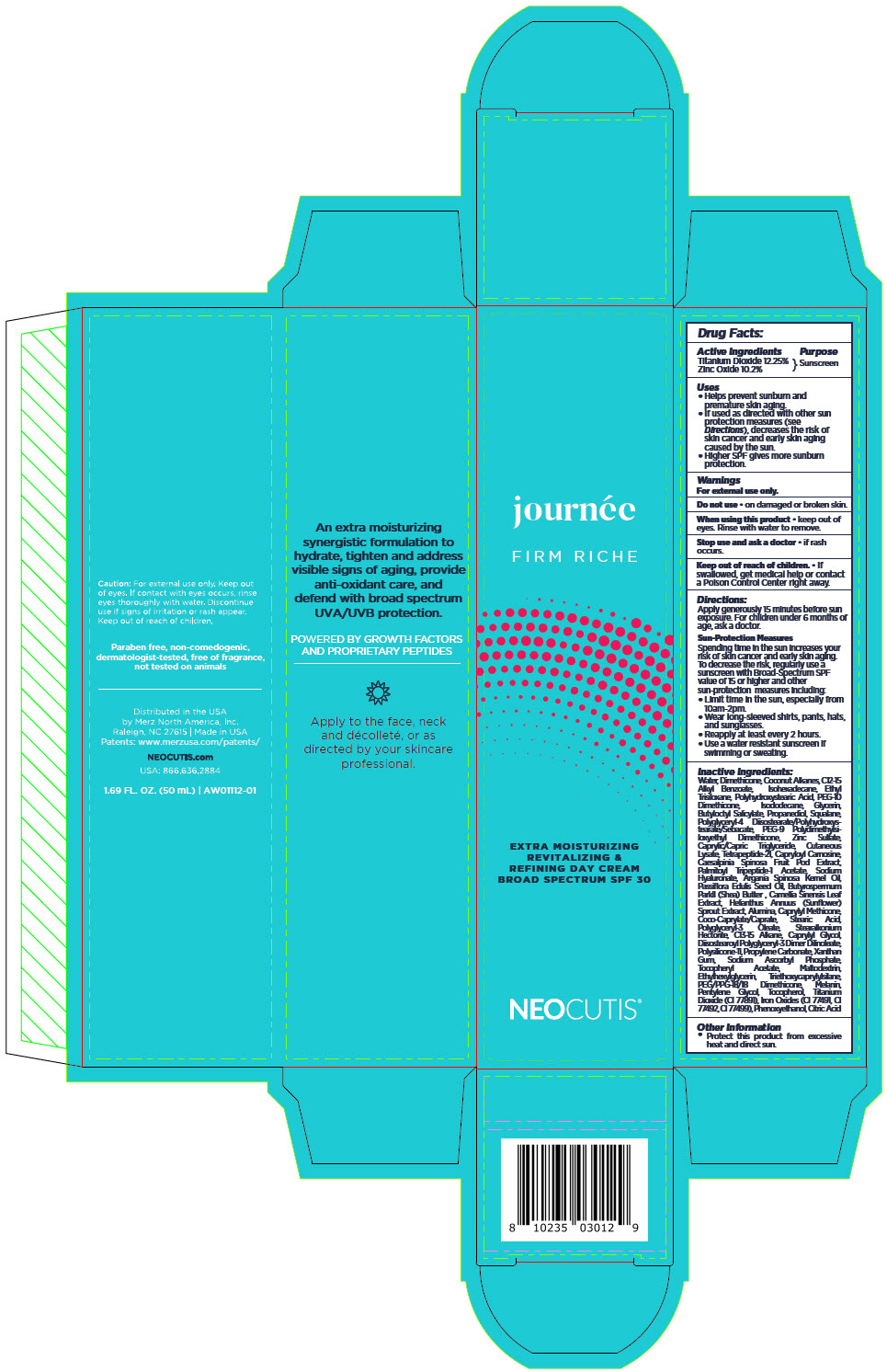 DRUG LABEL: Journee Firm Riche Broad Spectrum Sunscreen SPF 30
NDC: 46783-110 | Form: CREAM
Manufacturer: Merz North America, Inc.
Category: otc | Type: HUMAN OTC DRUG LABEL
Date: 20231023

ACTIVE INGREDIENTS: TITANIUM DIOXIDE 12.25 mg/1 mL; ZINC OXIDE 10.2 mg/1 mL
INACTIVE INGREDIENTS: WATER; Dimethicone; Coconut Alkanes; Alkyl (C12-15) Benzoate; Isohexadecane; Ethyl Trisiloxane; Polyhydroxystearic Acid (2300 MW); PEG-10 Dimethicone (600 CST); Isododecane; Glycerin; Butyloctyl Salicylate; Propanediol; Squalane; Polyglyceryl-4 diisostearate/polyhydroxystearate/sebacate; PEG-9 Polydimethylsiloxyethyl Dimethicone; Zinc Sulfate, Unspecified Form; Medium-Chain Triglycerides; Human Skin Proteins, Partially Hydrolyzed; Tetrapeptide-21; Carnosine; Caesalpinia Spinosa Fruit Pod; Palmitoyl Tripeptide-1 Acetate; Hyaluronate Sodium; Green Tea Leaf; Helianthus Annuus Sprout; Aluminum Oxide; Caprylyl Trisiloxane; Cocoyl Caprylocaprate; Stearic Acid; Polyglyceryl-3 Oleate; Stearalkonium Hectorite; C13-15 Alkane; Diisostearoyl Polyglyceryl-3 Dimer Dilinoleate; Dimethicone/Vinyl Dimethicone Crosspolymer (Soft Particle); Propylene Carbonate; Xanthan Gum; Sodium Ascorbyl Phosphate; .Alpha.-Tocopherol Acetate; Maltodextrin; Ethylhexylglycerin; Triethoxycaprylylsilane; PEG/PPG-18/18 Dimethicone; Melanin Synthetic (Tyrosine, Peroxide); Pentylene Glycol; Tocopherol; Ferric Oxide Red; Ferric Oxide Yellow; Ferrosoferric Oxide; Argan Oil; Caprylyl Glycol; Passiflora Edulis Seed Oil; Shea Butter; phenoxyethanol; Citric Acid Monohydrate

Journée Firm Riche Broad Spectrum Sunscreen SPF 30

Drug Facts:

Active Ingredients

Titanium Dioxide 12.25%
Zinc Oxide 10.2%

Purpose

Sunscreen

Uses

- Helps prevent sunburn and premature skin aging.
- If used as directed with other sun protection measures (see Directions), decreases the risk of skin cancer and early skin aging caused by the sun.
- Higher SPF gives more sunburn protection.

Warnings

For external use only.

Do not use

- on damaged or broken skin.

When using this product

- keep out of eyes. Rinse with water to remove.

Stop use and ask a doctor

- if rash occurs.

Keep out of reach of children.

- If swallowed, get medical help or contact a Poison Control Center right away.

Directions

Apply generously 15 minutes before sun exposure. For children under 6 months of age, ask a doctor.

Sun-Protection Measures

Spending time in the sun increases your risk of skin cancer and early skin aging. To decrease the risk, regularly use a sunscreen with Broad-Spectrum SPF value of 15 or higher and other sun-protection measures including:

- Limit time in the sun, especially from 10am-2pm.
- Wear long-sleeved shirts, pants, hats, and sunglasses.
- Reapply at least every 2 hours.
- Use a water resistant sunscreen if swimming or sweating.

Inactive Ingredients

Water, Dimethicone, Coconut Alkanes, C12-15 Alkyl Benzoate, Isohexadecane, Ethyl Trisiloxane, Polyhydroxystearic Acid, PEG-10 Dimethicone, Isododecane, Glycerin, Butyloctyl Salicylate, Propanediol, Squalane, Polyglyceryl-4 Diisostearate/Polyhydroxystearate/Sebacate, PEG-9 Polydimethylsiloxyethyl Dimethicone, Zinc Sulfate, Caprylic/Capric Triglyceride, Cutaneous Lysate, Tetrapeptide-21, Capryloyl Carnosine, Caesalpinia Spinosa Fruit Pod Extract, Palmitoyl Tripeptide-1 Acetate, Sodium Hyaluronate, Argania Spinosa Kernel Oil, Passiflora Edulis Seed Oil, Butyrospermum ParkII (Shea) Butter , Camellia Sinensis Leaf Extract, Helianthus Annuus (Sunflower) Sprout Extract, Alumina, Caprylyl Methicone, Coco-Caprylate/Caprate, Stearic Acid, Polyglyceryl-3 Oleate, Stearalkonium Hectorite, C13-15 Alkane, Caprylyl Glycol, Diisostearoyl Polyglyceryl-3 Dimer Dilinoleate, Polysilicone-11, Propylene Carbonate, Xanthan Gum, Sodium Ascorbyl Phosphate, Tocopheryl Acetate, Maltodextrin, Ethylhexylglycerin, Triethoxycaprylylsilane, PEG/PPG-18/18 Dimethicone, Melanin, Pentylene Glycol, Tocopherol, Titanium Dioxide (CI 77891), Iron Oxides (CI 77491, CI 77492, CI 77499), Phenoxyethanol, Citric Acid

Other Information

- Protect this product from excessive heat and direct sun.

Distributed in the USA
by Merz North America, Inc.
Raleigh, NC 27615

PRINCIPAL DISPLAY PANEL - 50 mL Bottle Carton

journée
FIRM RICHE

EXTRA MOISTURIZING
REVITALIZING &
REFINING DAY CREAM
BROAD SPECTRUM SPF 30

NEOCUTIS®